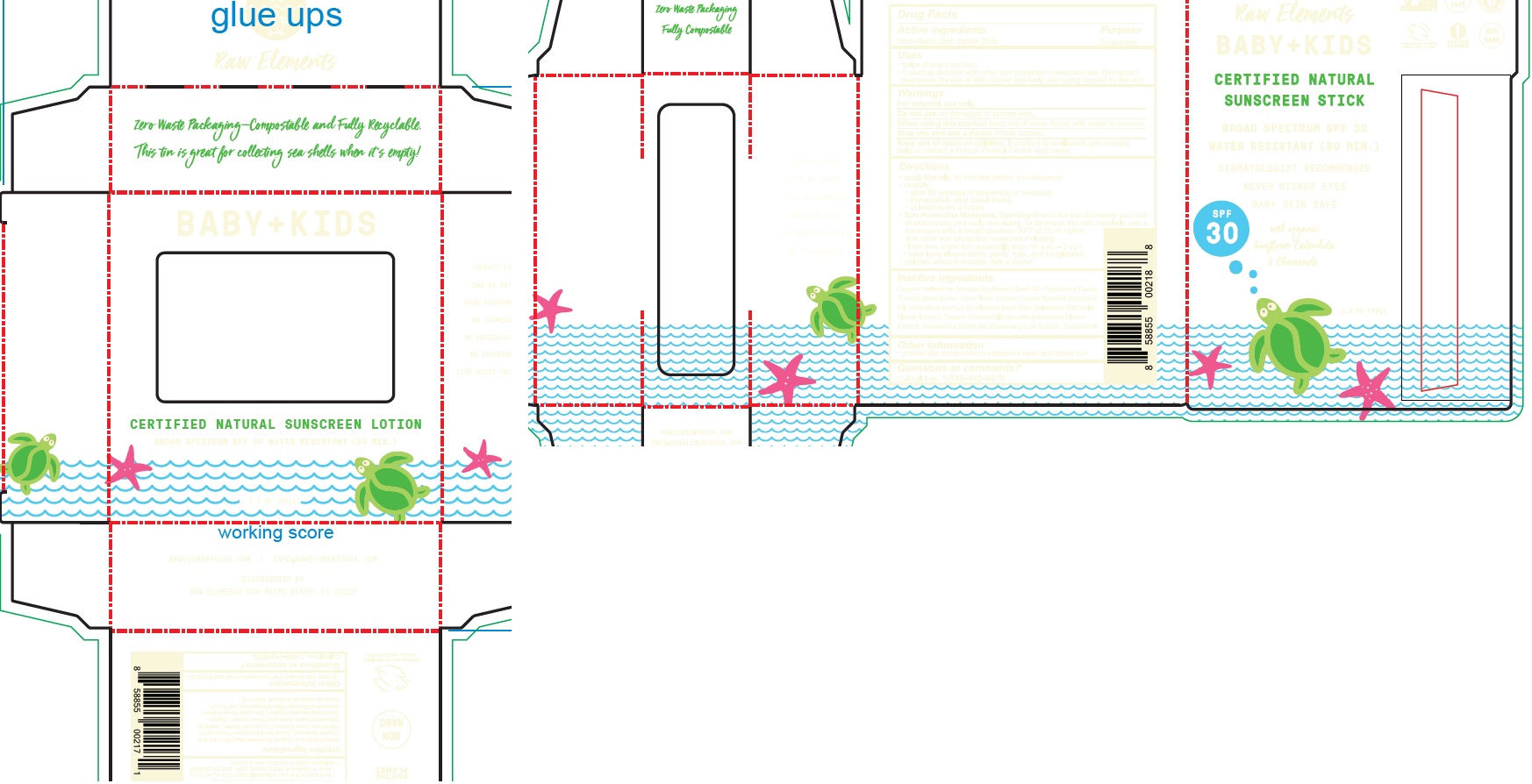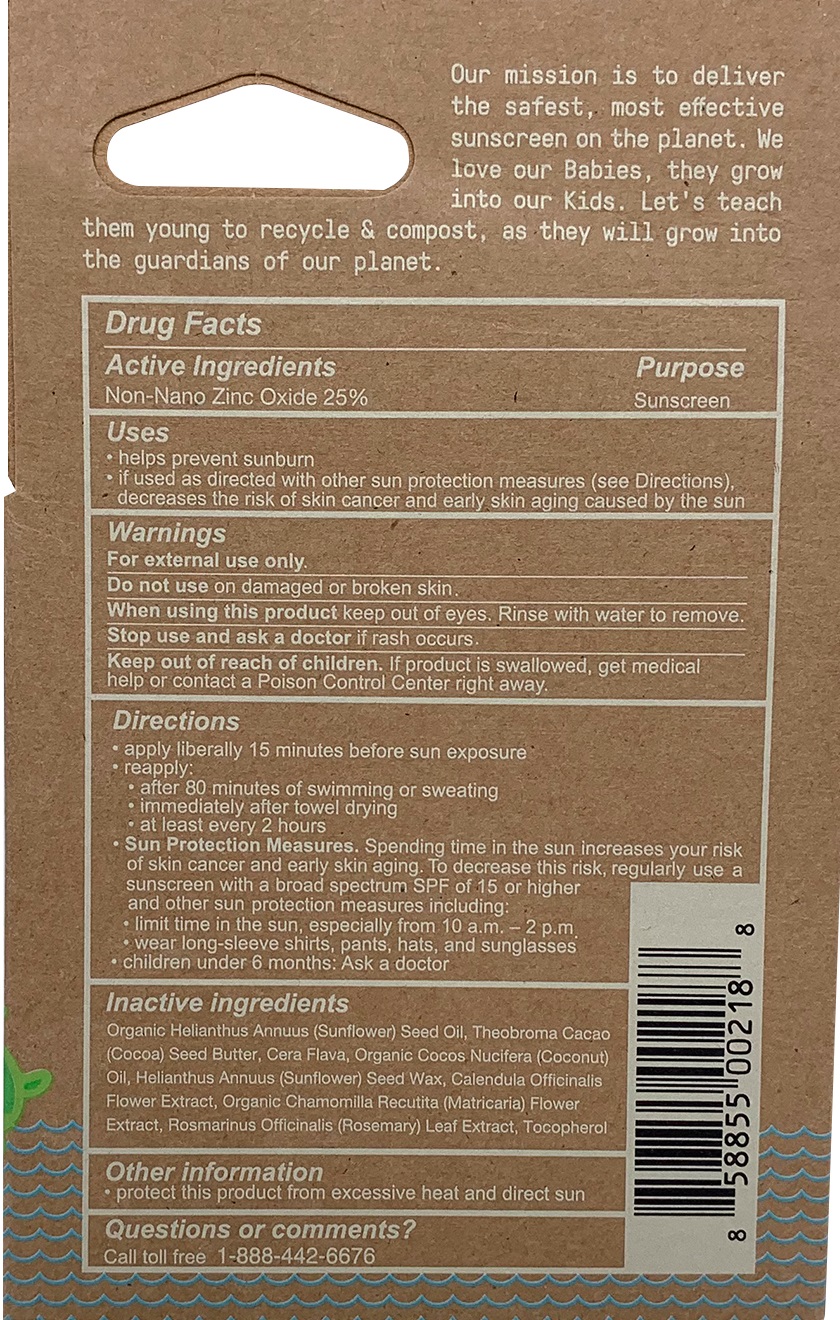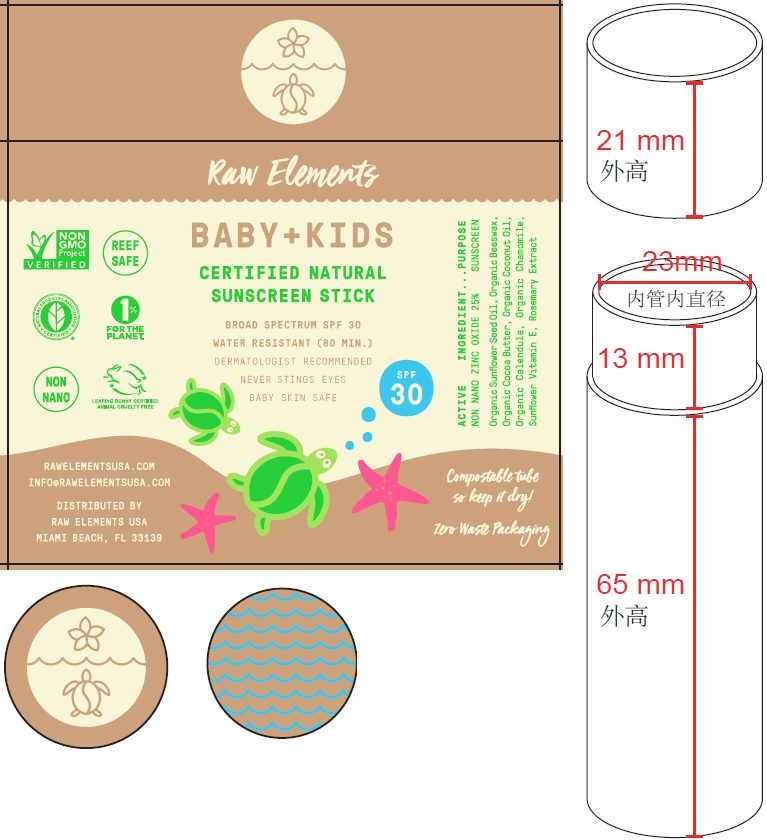 DRUG LABEL: Raw Elements Baby Kids Broad Spectrum SPF30 Sunscreen
NDC: 70680-306 | Form: STICK
Manufacturer: Raw Elements LLC
Category: otc | Type: HUMAN OTC DRUG LABEL
Date: 20231109

ACTIVE INGREDIENTS: ZINC OXIDE 250 mg/1 g
INACTIVE INGREDIENTS: SUNFLOWER OIL; COCOA BUTTER; COCONUT OIL; HELIANTHUS ANNUUS SEED WAX; CALENDULA OFFICINALIS FLOWER; MATRICARIA CHAMOMILLA; ROSEMARY; TOCOPHEROL

Raw Elements Baby+Kids Broad Spectrum SPF30 Sunscreen Stick

Active Ingredients

Non-Nano Zinc Oxide 25%

Purpose

Sunscreen

Uses

- helps prevent sunburn
- If used as directed with other sun protection measures (see Directions), decreases the risk of skin cancer and early skin aging caused by the sun

Warnings

For external use only.

Do not use

on damaged or broken skin.

When using this product

keep out of eyes. Rinse with water to remove.

Stop use and ask a doctor

if rash occurs.

Keep out of reach of children.

If product is swallowed, get medical help or contact a Poison Control Center right away.

Directions

- apply liberally 15 minutes before sun exposure
- reapply:
- after 80 minutes of swimming or sweating
- immediately after towel drying
- at least every 2 hours
- Spending time in the sun increases your risk of skin cancer and early skin aging. To decrease this risk, regularly use a sunscreen with a broad spectrum SPF of 15 or higher and other sun protection measures including: Sun Protection Measures.
- limit time in the sun, especially from 10 a.m.-2 p.m.
- wear long-sleeve shirts, pants, hats, and sunglasses
- children under 6 months: Ask a doctor

Inactive ingredients

Organic Helianthus Annuus (Sunflower) Seed Oil, Theobroma Cacao (Cocoa) Seed Butter, Cera Flava, Organic Cocos Nucifera (Coconut) Oil, Helianthus Annuus (Sunflower) Seed wax, Calendula Officinalis Flower Extract, Organic Chamomilla Recutita (Matricaria) Flower Extract, Rosmarinus Officinalis (Rosemary) Leaf Extract, Tocopherol

Other information

- protect this product from excessive heat and direct sun

Questions or comments?

Call toll free 1-888-442-6676